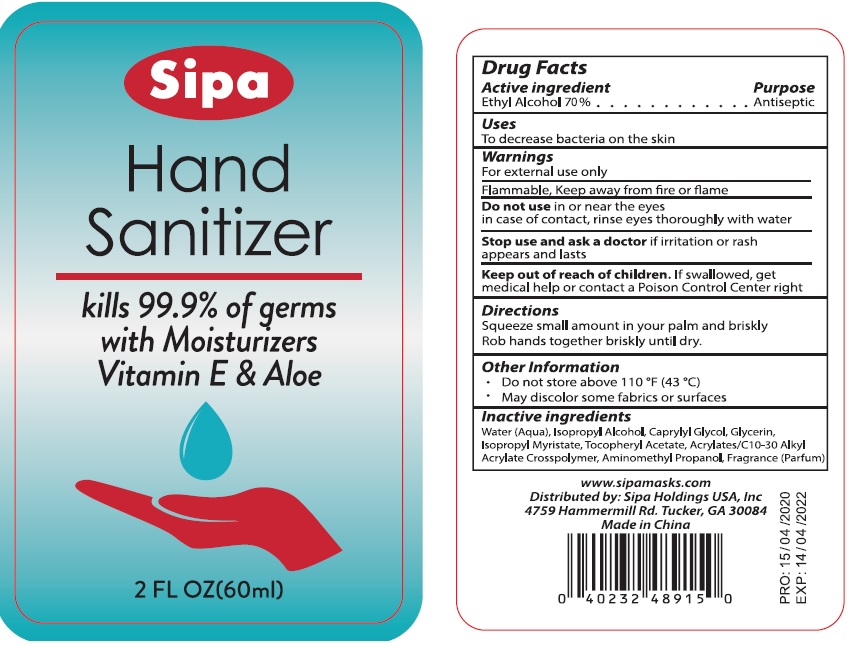 DRUG LABEL: Sipa Hand Sanitizer With Moisturizers Vitamin E and Aloe
NDC: 52174-014 | Form: GEL
Manufacturer: Ningbo BST Clean And Care Products Co., Ltd
Category: otc | Type: HUMAN OTC DRUG LABEL
Date: 20200514

ACTIVE INGREDIENTS: alcohol 70 mL/100 mL
INACTIVE INGREDIENTS: WATER; CAPRYLYL GLYCOL; ISOPROPYL MYRISTATE; .ALPHA.-TOCOPHEROL ACETATE, D-; AMINOMETHYLPROPANOL; CARBOMER COPOLYMER TYPE A; GLYCERIN

Drug facts

Active ingredient Purpose

Ethyl Alcohol 70% ... Antimicrobial

PURPOSE

To decrease bacteria on the skin.

KEEP OUT OF REACH OF CHILDREN

If swallowed, get medical help or contact a Poison Control Center right away.

INDICATIONS AND USAGE

Squeeze small amount in your palm and briskly

Rob hands together briskly until dry.

WARNINGS

For external use only.
Flammable. Keep away from fire or flame.

Do not use in or near the eyes. In case of contact, rinse thoroghly with water

Stop using and ask a doctor, if irritation or rash appears and lasts.

Other information:

- Do not store above 110℉（43℃）
- May discolor certain fabrics or surfaces.

DOSAGE AND ADMINISTRATION

Rob hands together briskly until dry.

INACTIVE INGREDIENT

Water, Isopropyl Alcohol, Caprylyl Glycol, Glycerin, Isopropyl Myristate, Tocopheryl Acetate, Acrylates/C10-30 Alkyl Acrylate Crosspolymer, Aminomethul Propanol, Fragrance (Pparfum)